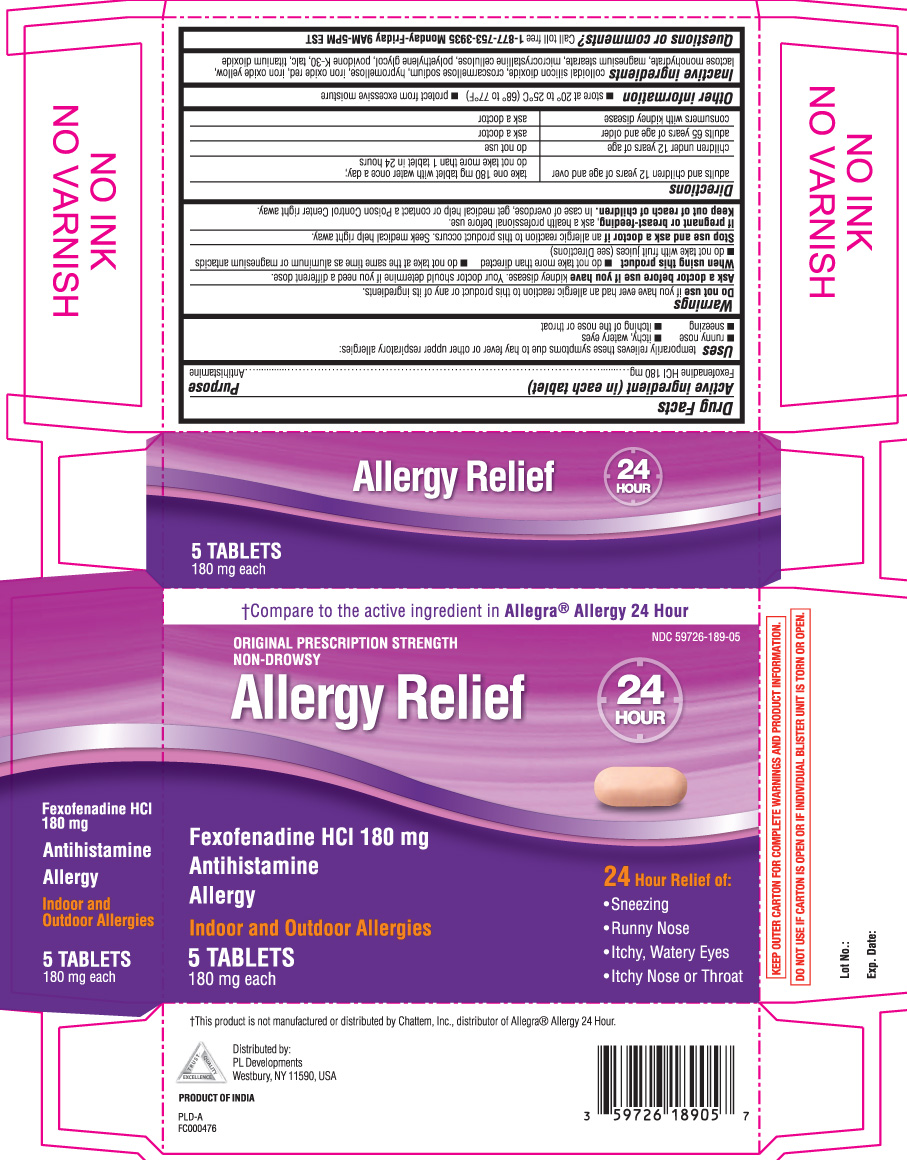 DRUG LABEL: Allergy Relief
NDC: 59726-189 | Form: TABLET
Manufacturer: P and L Development of New York Corporation
Category: otc | Type: HUMAN OTC DRUG LABEL
Date: 20121220

ACTIVE INGREDIENTS: FEXOFENADINE HYDROCHLORIDE 180 mg/1 1
INACTIVE INGREDIENTS: SILICON DIOXIDE; CROSCARMELLOSE SODIUM; HYPROMELLOSES; FERRIC OXIDE RED; FERRIC OXIDE YELLOW; LACTOSE MONOHYDRATE; MAGNESIUM STEARATE; CELLULOSE, MICROCRYSTALLINE; POLYETHYLENE GLYCOLS; POVIDONE K30; TALC; TITANIUM DIOXIDE

DRUG FACTS

Active ingredient (in each tablet)

Fexofenadine HCl 180 mg

Purpose

Antihistamine

Uses

temporarily relieves these symptoms due to hay fever or other upper respiratory allergies:

- runny nose
- itchy, watery eyes
- sneezing
- itching of the nose or throat

Warnings

Do not use

if you have ever had an allergic reaction to this product or any of its ingredients.

Ask a doctor before use if you have

kidney disease. Your doctor should determine if you need a different dose.

When using this product

- do not take more than directed
- do not take at the same time as aluminum or magnesium antacids
- do not take with fruit juices (see Directions)

Stop use and ask a doctor if

an allergic reaction to this product occurs. Seek medical help right away.

If pregnant or breast-feeding,

ask a health professional before use.

Keep out of reach of children.

In case of overdose, get medical help or contact a Poison Control Center right away.

Directions

adults and children 12 years of age and over | take one 180 mg tablet with water once a day; do not take more than 1 tablet in 24 hours
children under 12 years of age | do not use
adults 65 years of age and older | ask a doctor
consumers with kidney disease | ask a doctor

Other information

- store at 20°-25°C (68°-77°F)
- protect from excessive moisture

Inactive ingredients

colloidal silicon dioxide, croscarmellose sodium, hypromellose, iron oxide red, iron oxide yellow, lactose monohydrate, magnesium stearate, microcrystalline cellulose, polyethylene glycol, povidone k-30, talc, titanium dioxide.

Questions or comments?

call toll free 1-877-753-3935 Monday- Friday 9AM- 5PM EST

Package/Label Principal Display Panel

†Compare to the active ingredient in Allegra® Allergy 24 hour

ORIGINAL PRESCRIPTION STRENGTH

NON-DROWSY

ALLERGY RELIEF

Fexofenadine HCl 180 mg

Antihistamine

ALLERGY

Indoor and outdoor Allergies

24 Hour Relief of:

- sneezing
- runny nose
- itchy, watery eyes
- itchy nose or throat

†This product is not manufactured or distributed by Chattem Inc., distributor of Allegra® Allergy 24 hour

KEEP OUTER CARTON FOR COMPLETE WARNINGS AND PRODUCT INFORMATION.

DO NOT USE IF CARTON IS OPEN OR IF INDIVIDUAL BLISTER UNIT IS TORN OR OPEN.

Distributed by: PL Developments

200 hicks street

westbury NY 11590

PRODUCT OF INDIA

Product Label

Fexofenadine HCl 180 mg